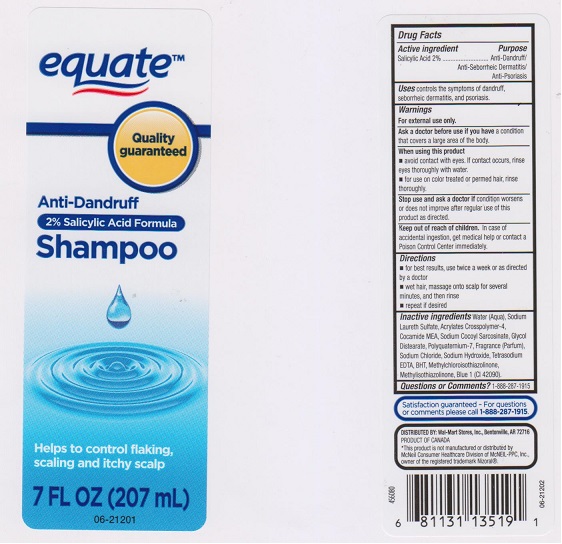 DRUG LABEL: EQUATE ANTI DANDRUFF
NDC: 49035-450 | Form: SHAMPOO
Manufacturer: WAL-MART STORES INC
Category: otc | Type: HUMAN OTC DRUG LABEL
Date: 20160229

ACTIVE INGREDIENTS: SALICYLIC ACID 20 mg/1 mL
INACTIVE INGREDIENTS: WATER; SODIUM LAURETH-3 SULFATE; CARBOMER COPOLYMER TYPE A (ALLYL PENTAERYTHRITOL CROSSLINKED); COCO MONOETHANOLAMIDE; SODIUM COCOYL SARCOSINATE; GLYCOL DISTEARATE; POLYQUATERNIUM-7 (70/30 ACRYLAMIDE/DADMAC; 1600000 MW); SODIUM CHLORIDE; SODIUM HYDROXIDE; EDETATE SODIUM; BUTYLATED HYDROXYTOLUENE; METHYLCHLOROISOTHIAZOLINONE; METHYLISOTHIAZOLINONE; FD&C BLUE NO. 1

DRUG FACTS

Active ingredient

Salicylic Acid 2%

Purpose

Anti-Dandruff/Anti-Seborrheic Dermatitis/Anti-Psoriasis

Uses

controls the symptoms of dandruff, seborrheic dermatitis, and psoriasis.

Warnings

For external use only.

Ask a doctor before use if you have

a condition that covers a large area of the body.

When using this product

- avoid contact with eyes. If contact occurs, rinse eyes thoroughly with water.
- for use on color treated or permed hair, rinse thoroughly.

Stop use and ask a doctor if

condition worsens or does not improve after regular use of this product as directed.

Keep out of reach of children.

In case of accidental ingestion, get medical help or contact a Poison Control Center immediately.

Directions

- for best results, use twice a week or as directed by a doctor.
- wet hair, massage onto scalp for several minutes, and then rinse.
- repeat if desired.

Inactive ingredients

Water (Aqua), Sodium Laureth Sulfate, Acrylates Crosspolymer-4, Cocamide MEA, Sodium Cocoyl Sarcosinate, Glycol Distearate, Polyquaternim-7, Fragrance (Parfum), Sodium Chloride, Sodium Hydroxide, Tetrasodium EDTA, BHT, Methylchloroisothiazolinone, Methylisothiazolinone, Blue 1 (CI 42090).

Questions or Comments?

1-888-287-1915